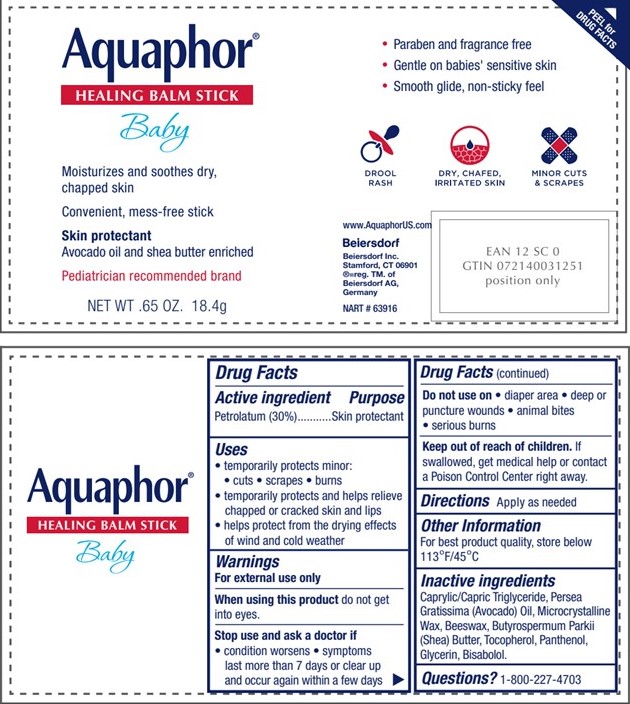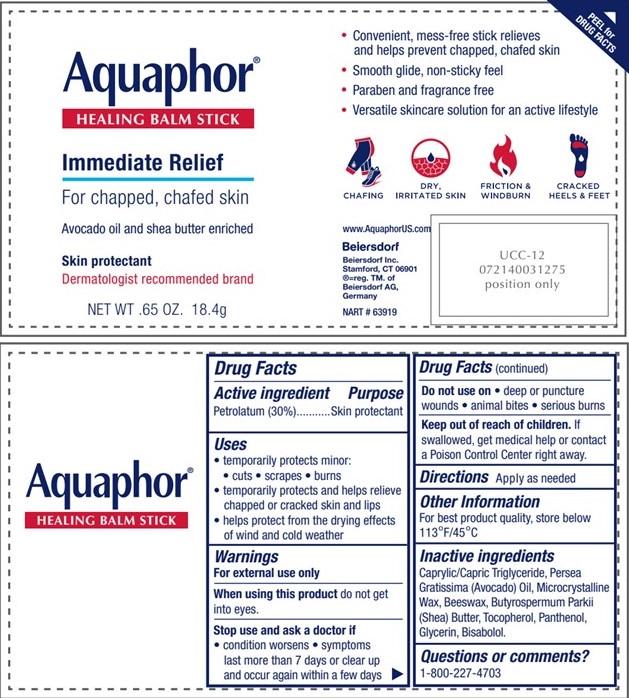 DRUG LABEL: Aquaphor Healing Balm Stick
NDC: 10356-125 | Form: OINTMENT
Manufacturer: Beiersdorf Inc
Category: otc | Type: HUMAN OTC DRUG LABEL
Date: 20251216

ACTIVE INGREDIENTS: PETROLATUM 30 g/100 g
INACTIVE INGREDIENTS: SHEA BUTTER; GLYCERIN; PANTHENOL; LEVOMENOL; AVOCADO OIL; MICROCRYSTALLINE WAX; TOCOPHEROL; MEDIUM-CHAIN TRIGLYCERIDES; YELLOW WAX

Aquaphor Healing Balm Stick

ACTIVE INGREDIENT

Petrolatum 30%

PURPOSE

Skin Protectant

Uses

• temporarily protects minor: • cuts • scrapes • burns
• temporarily protects and helps relieve chapped or cracked skin and lips
• helps protect from the drying effects of wind and cold weather

Stop use and ask a doctor if • condition worsens
• symptoms last more than 7 days or clear up and occur
again within a few days

Do not use on

• deep or puncture wounds • animal bites
• serious burns

Keep out of reach of children. If swallowed, get medical help
or contact a Poison Control Center right away.

INACTIVE INGREDIENT

Inactive ingredients: Caprylic/Capric Triglyceride, Persea Gratissima (Avocado) Oil, Microcrystalline Wax, Beeswax, Butyrospermum Parkii (Shea) Butter, Tocopherol, Panthenol, Glycerin, Bisabolol.

Questions or comments?
1-800-227-4703

Directions

• apply as needed

PACKAGE LABEL

Aquaphor Healing Balm Stick

Immediate Relief

For chapped, chafed skin

Avocado oil and shea butter enriched

Skin protectant

Dematologist recommended brand

Aquaphor Healing Balm Stick

Baby

Moisturizes and soothes ddry, chapped skin

Convenient mess-free stick

Skin Protectant

Avocado and Shea butter enriched

Pediatrician recommended brand